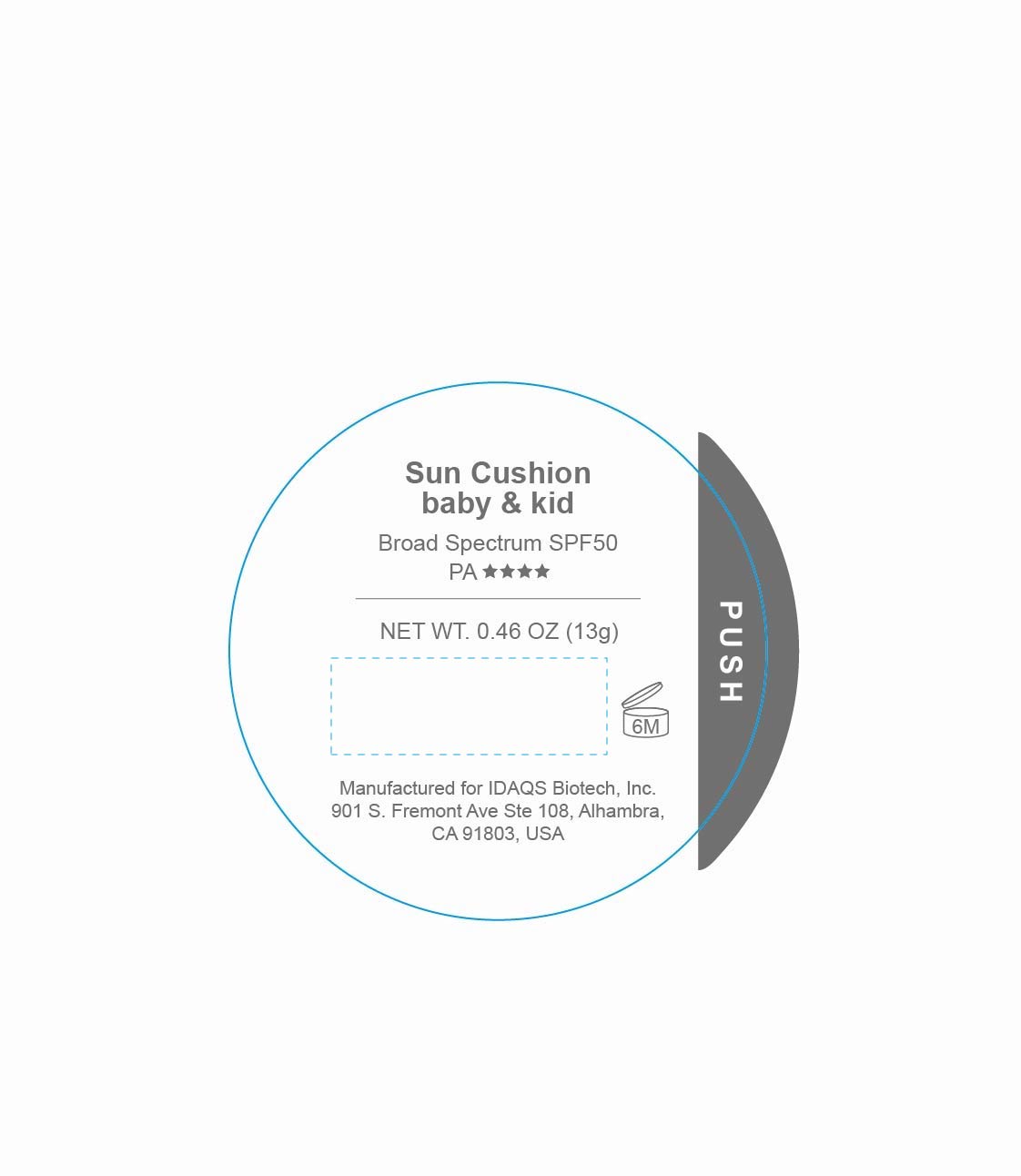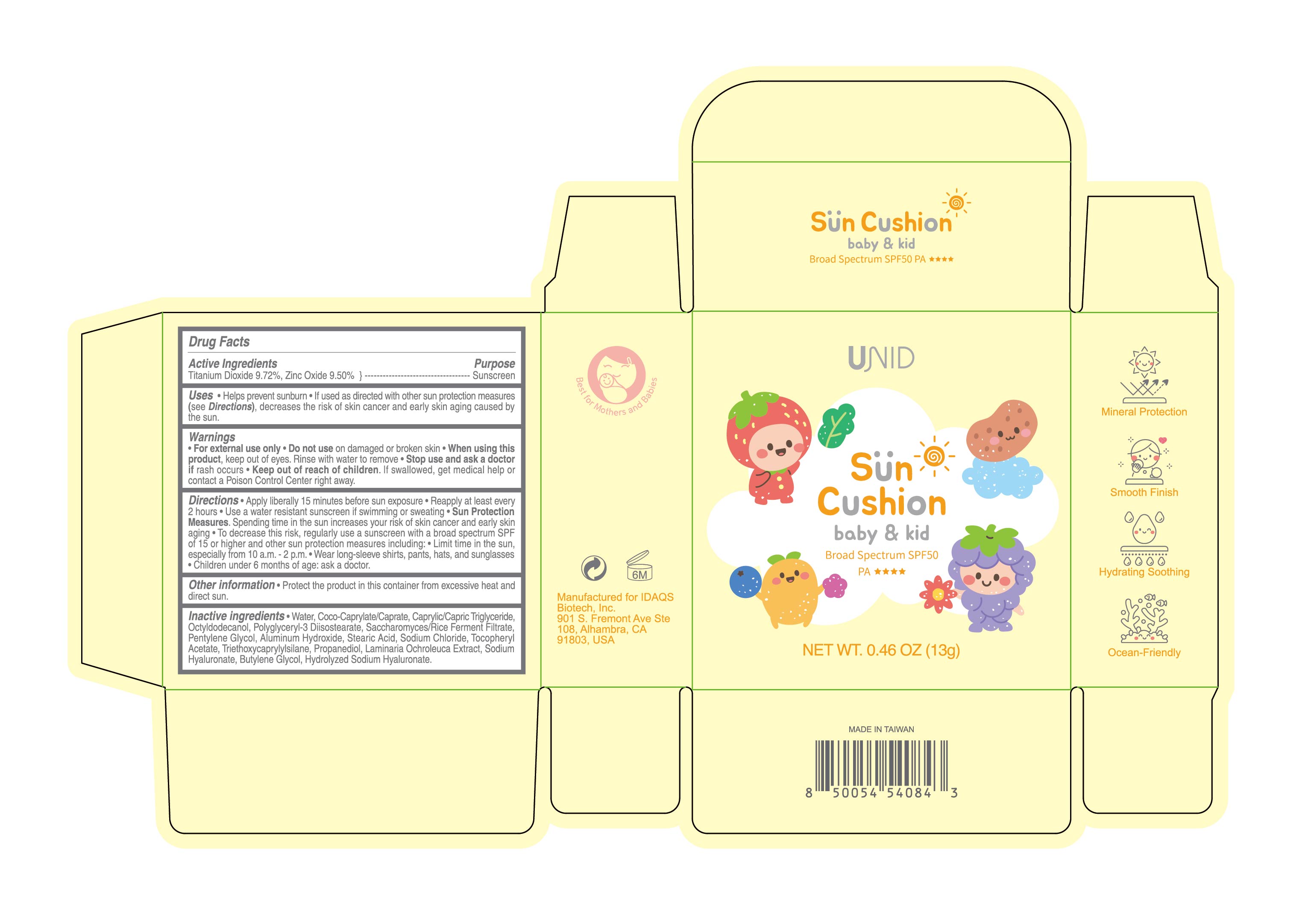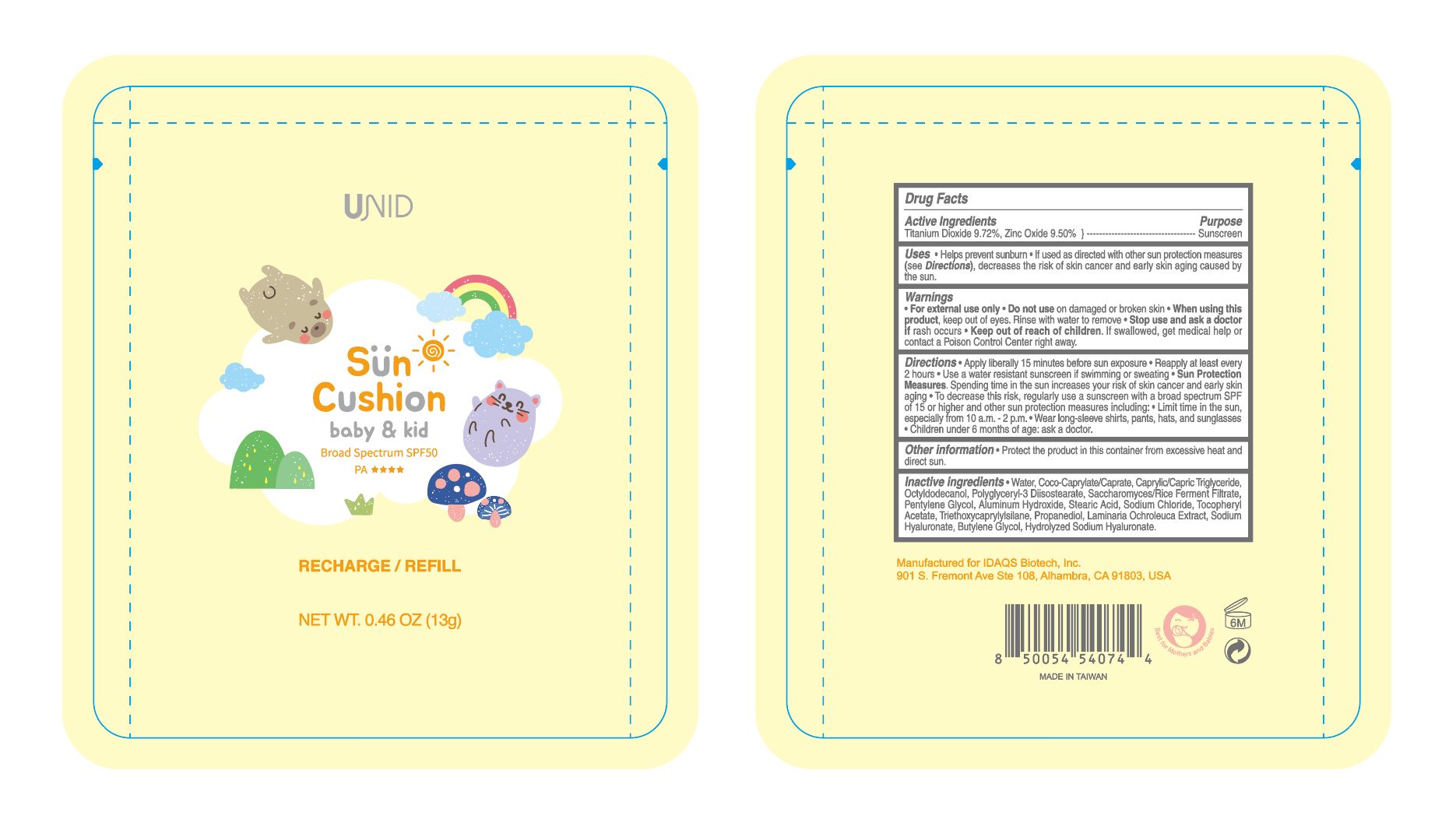 DRUG LABEL: UNID Sun Cushion baby and kid
NDC: 83119-241 | Form: LOTION
Manufacturer: Sage Pharmaceuticals Inc
Category: otc | Type: HUMAN OTC DRUG LABEL
Date: 20251223

ACTIVE INGREDIENTS: TITANIUM DIOXIDE 9.72 g/100 g; ZINC OXIDE 9.5 g/100 g
INACTIVE INGREDIENTS: LAMINARIA OCHROLEUCA; POLYGLYCERYL-3 DIISOSTEARATE; STEARIC ACID; PENTYLENE GLYCOL; COCO-CAPRYLATE/CAPRATE; PROPANEDIOL; SODIUM HYALURONATE; BUTYLENE GLYCOL; WATER; CAPRYLIC/CAPRIC TRIGLYCERIDE; OCTYLDODECANOL; SACCHAROMYCES CEREVISIAE; ALUMINUM HYDROXIDE; SODIUM CHLORIDE; TRIETHOXYCAPRYLYLSILANE; .ALPHA.-TOCOPHEROL ACETATE

UNID Sun Cushion baby and kid SPF50

Active Ingredients

Titanium Dioxide 9.72%

Zinc Oxide 9.50%

Purpose

Sunscreen

Uses

- Helps prevent sunburn
- If used as directed with other sun protection measures (see Directions), decreases the risk of skin cancer and early skin aging caused by the sun

Warnings

For external use only

Do not use on damaged or broken skin

When using this product, keep out of eyes. Rinse with water to remove.

Stop use and ask a doctor if rash occurs

Keep out of reach of children. If swallowed, get medical help or contact a Poison Control Center right away.

Directions

- Apply liberally 15 minutes before sun exposure
- Reapply at least every 2 hours
- Use a water-resistant sunscreen if swimming or sweating
- Sun Protection Measures. Spending time in the sun increases your risk of skin cancer and early skin aging.
- To decrease this risk, regularly use a sunscreen with a broad spectrum SPF of 15 or higher and other sun protection measures including:
- Limit time in the sun, especially from 10 a.m.–2 p.m.
- Wear long-sleeve shirts, pants, hats, and sunglasses
- Children under 6 months of age: ask a doctor.

Other information

Protect the product in this container from excessive heat and direct sun.

Inactive Ingredients

Water, Coco-Caprylate/Caprate, Caprylic/Capric Triglyceride, Octyldodecanol, Polyglyceryl-3 Diisostearate, Saccharomyces/Rice Ferment Filtrate, Pentylene Glycol, Aluminum Hydroxide, Stearic Acid, Sodium Chloride, Tocopheryl Acetate, Triethoxycaprylylsilane, Propanediol, Laminaria Ochroleuca Extract, Sodium Hyaluronate, Butylene Glycol, Hydrolyzed Sodium Hyaluronate.

Sage Pharmaceuticals Inc

Product of Taiwan

Manufactured for IDAQS Biotech, Inc.

Distributed by Beauty River International Inc.
901 S. Fremont Ave 108, Alhambra, CA 91803-4703, USA